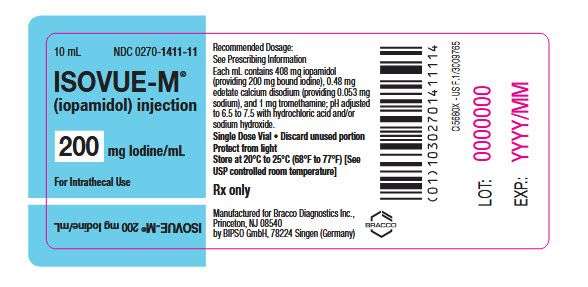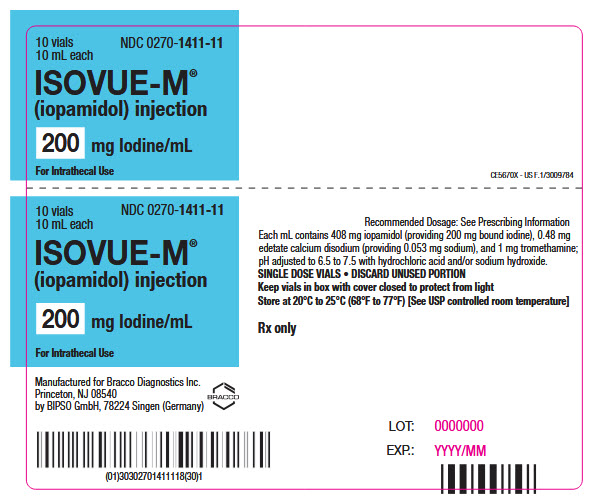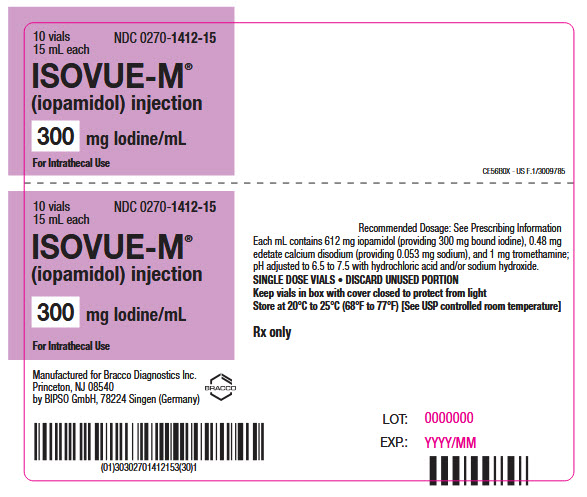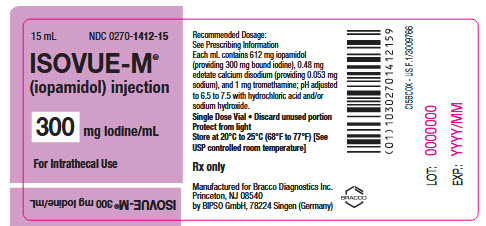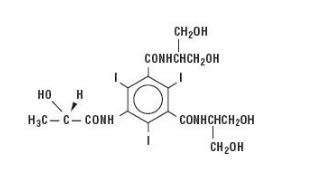 DRUG LABEL: ISOVUE-M
NDC: 0270-1411 | Form: INJECTION, SOLUTION
Manufacturer: Bracco Diagnostics Inc
Category: prescription | Type: HUMAN PRESCRIPTION DRUG LABEL
Date: 20260210

ACTIVE INGREDIENTS: IOPAMIDOL 408 mg/1 mL
INACTIVE INGREDIENTS: tromethamine 1 mg/1 mL; edetate calcium disodium 0.26 mg/1 mL

HIGHLIGHTS OF PRESCRIBING INFORMATION

These highlights do not include all the information needed to use ISOVUE-M safely and effectively. See full prescribing information for ISOVUE-M.
ISOVUE®-M (iopamidol) injection, for intrathecal use
Initial U.S. Approval: 1985

Recent Major Changes

Indications and Usage, CT cerebral ventriculography (1)-Removed | 1/2026

1 INDICATIONS AND USAGE

ISOVUE-M is a radiographic contrast agent indicated for:

- Lumbar and thoracic myelography and computed tomography (CT) myelography in adults and pediatric patients aged 2 years and older
- Cervical and total columnar myelography in adults
- CT cisternography in adults (1)

Specific concentrations of ISOVUE-M are recommended for each type of imaging procedure. (2.2, 2.3)

2 DOSAGE AND ADMINISTRATION

- Individualize the volume and concentration of ISOVUE-M according to the specific dosing tables based on patient age, body weight, and study to be performed. (2.2, 2.3)
- See full prescribing information for important dosage and administration information. (2.1)

3 DOSAGE FORMS AND STRENGTHS

Injection: 200 mg Iodine/mL and 300 mg Iodine/mL in single-dose vials (3)

4 CONTRAINDICATIONS

None (4)

5 WARNINGS AND PRECAUTIONS

- Hypersensitivity Reactions: Life-threatening or fatal reactions can occur. Always have emergency resuscitation equipment and trained personnel available. (5.1)
- Acute Kidney Injury: Acute injury including renal failure can occur. Use the lowest dose and maintain adequate hydration to minimize risk. (5.2)
- Cardiovascular Adverse Reactions: Hemodynamic disturbances including shock and cardiac arrest may occur during or after ISOVUE-M administration. (5.4)
- Thyroid Dysfunction in Pediatric Patients 0 Years to 3 Years of Age: Individualize thyroid function monitoring based on risk factors such as prematurity. (5.6)

6 ADVERSE REACTIONS

Most common adverse reactions (incidence > 1%) are headache, nausea, vomiting, back pain, leg pain, neck pain, and hypotension. (6.1)

To report SUSPECTED ADVERSE REACTIONS, contact Bracco Diagnostics Inc. at 1-800-257-5181 or FDA at 1-800-FDA-1088 or www.fda.gov/medwatch.

8 USE IN SPECIFIC POPULATIONS

Lactation: A lactating woman may pump and discard breast milk for 10 hours after ISOVUE-M administration. (8.2)

FULL PRESCRIBING INFORMATION

1 INDICATIONS AND USAGE

ISOVUE-M is indicated for:

- Lumbar and thoracic myelography, and computed tomography (CT) myelography in adults and pediatric patients aged 2 years and older
- Cervical and total columnar myelography and CT myelography in adults
- CT cisternography in adults

Specific concentrations of ISOVUE-M are recommended for each type of imaging procedure [see Dosage and Administration (2.2, 2.3)].

2 DOSAGE AND ADMINISTRATION

2.1 Important Dosage and Administration Information

- ISOVUE-M is for intrathecal use only.
- Specific concentrations of ISOVUE-M are recommended for each type of imaging procedure [see Dosage and Administration (2.2, 2.3)].
- Individualize the volume, concentration, and injection rate of ISOVUE-M according to the dosing tables [see Dosage and Administration (2.2, 2.3)]. Consider factors such as age, body weight, anticipated pathology and degree and extent of opacification required, structure(s) or area to be examined, concomitant medical conditions, and imaging equipment and technique to be employed.
- Hydrate patients prior to and following ISOVUE-M administration [see Warnings and Precautions (5.2)].
- Use aseptic technique for all handling and administration of ISOVUE-M.
- ISOVUE-M may be administered at either body temperature (37°C, 98.6°F) or room temperature (20°C to 25°C, 68°F to 77°F).
- Visually inspect ISOVUE-M for particulate matter and discoloration prior to administration whenever the solution and container permit. Do not administer ISOVUE-M if particulate matter or discoloration are observed.
- Do not mix ISOVUE-M with other drugs.
- ISOVUE-M is packaged in a single-dose vial and intended for one procedure only. Discard any unused portion.

2.2 Recommended Dosage for Intrathecal Procedures in Adults

- The recommended doses in adults are shown in Table 1.
- Administer over 1 minute to 2 minutes.
- Allow at least 48 hours before repeat administration to avoid overdose; however, whenever possible, 5 days to 7 days is recommended.
- If CT myelography is performed, delay imaging by at least 4 hours to reduce the degree of contrast.

Table 1: Recommended Concentrations and Volumes of ISOVUE-M for Intrathecal Procedures in Adults
Imaging Procedure | Concentration (mg Iodine/mL) | Volume to Administer | Injection Type
Lumbar and thoracic myelography | 200 | 10 mL to 15 mL | Lumbar
Cervical myelography | 200 | 10 mL to 15 mL | Lumbar
Cervical myelography | 200 | 10 mL | Lateral cervical
Cervical myelography | 300 | 10 mL | Lumbar
Total columnar myelography | 300 | 10 mL | Lumbar
CT cisternography | 200 | 4 mL to 6 mL | Lumbar

2.3 Recommended Dosage for Intrathecal Procedures in Pediatric Patients Aged 2 Years and Older

- The recommended doses based on age for pediatric patients aged 2 years and older are shown in Table 2.
- Administer over 1 minute to 2 minutes.
- Allow at least 48 hours before repeat administration to avoid overdose; however, whenever possible, 5 days to 7 days is recommended.
- If CT myelography is performed, delay imaging by at least 4 hours to reduce the degree of contrast.

Table 2: Recommended Concentrations and Volumes of ISOVUE-M Based on Age for Intrathecal Procedures in Pediatric Patients Aged 2 Years and Older
Imaging Procedure | Age | Concentration (mg Iodine/mL) | Volume to Administer | Injection Type
Lumbar and thoracic myelography | 2 years to 7 years | 200 | 7 mL to 9 mL | Lumbar
Lumbar and thoracic myelography | 8 years to 12 years | 200 | 8 mL to 11 mL | Lumbar
Lumbar and thoracic myelography | 13 years and older | 200 | 10 mL to 12 mL | Lumbar

3 DOSAGE FORMS AND STRENGTHS

Injection: clear, colorless to pale yellow solution available in two concentrations of iodine:

Concentration (mg of Iodine/mL) | Package Size | Package Type
200 | 10 mL | Single-Dose Vial
300 | 15 mL | Single-Dose Vial

4 CONTRAINDICATIONS

None.

5 WARNINGS AND PRECAUTIONS

5.1 Hypersensitivity Reactions

ISOVUE-M can cause life-threatening or fatal hypersensitivity reactions including anaphylaxis. Manifestations include respiratory arrest, laryngospasm, bronchospasm, angioedema, and shock [see Adverse Reactions (6.2)]. Most severe reactions develop shortly after the start of injection (e.g., within 1 to 3 minutes), but delayed reactions can also occur. There is increased risk of hypersensitivity reactions in patients with a history of previous reactions to contrast agents, and known allergic disorders (i.e., bronchial asthma, allergic rhinitis, and food allergies) or other hypersensitivities.

Premedication with antihistamines or corticosteroids does not prevent serious life-threatening reactions, but may reduce their incidence and severity. Obtain a history of allergy or hypersensitivity reactions to iodinated contrast agents and always have emergency resuscitation equipment and trained personnel available prior to ISOVUE-M administration. Monitor all patients for hypersensitivity reactions.

5.2 Acute Kidney Injury

Acute kidney injury, including renal failure, may occur after administration of iodinated contrast agents. Risk factors include pre-existing renal insufficiency, dehydration, diabetes mellitus, congestive heart failure, advanced vascular disease, elderly age, concomitant use of nephrotoxic or diuretic medications, multiple myeloma or other paraproteinemias, and repetitive or large doses of iodinated contrast agents.

Use the lowest dose of ISOVUE-M, especially in patients with risk factors for acute kidney injury. Adequately hydrate patients prior to and following ISOVUE-M administration.

5.3 Increased Risk of Seizures

Focal and generalized motor seizures have been reported after intrathecal use of iodinated contrast agents including ISOVUE-M. In several of the cases, higher than recommended doses were administered.

Use of medications that may lower the seizure threshold (phenothiazine derivatives, including those used for their antihistaminic properties; tricyclic antidepressants; MAO inhibitors; CNS stimulants; analeptics; antipsychotic agents) should be carefully evaluated. Consider discontinuing these agents at least 48 hours before and for at least 24 hours following intrathecal administration of ISOVUE-M.

5.4 Cardiovascular Adverse Reactions

Iodinated contrast agents increase the circulatory osmotic load and may induce acute or delayed hemodynamic disturbances in patients with congestive heart failure, severely impaired renal function, combined renal and hepatic disease, and combined renal and cardiac disease, particularly when repetitive or large doses are administered. Fatal cardiovascular reactions have occurred mostly within 10 minutes of injection of iodinated contrast agent by an intravascular route; the main feature was cardiac arrest with cardiovascular disease as the main underlying factor. Hypotensive collapse and shock have occurred.

The administration of iodinated contrast agent may cause pulmonary edema in patients with heart failure. Based upon published reports, deaths associated with the administration of iodinated contrast agents range from 6.6 per 1 million (0.00066 percent) to 1 in 10,000 patients (0.01 percent).

Use the lowest necessary dose of ISOVUE-M in patients with congestive heart failure and always have emergency resuscitation equipment and trained personnel available. Monitor all patients for severe cardiovascular reactions.

5.5 Thyroid Storm in Patients with Hyperthyroidism

Thyroid storm has occurred after the use of iodinated contrast agents in patients with hyperthyroidism, or with an autonomously functioning thyroid nodule. Evaluate the risk in such patients before use of ISOVUE-M.

5.6 Thyroid Dysfunction in Pediatric Patients 0 Years to 3 Years of Age

Thyroid dysfunction characterized by hypothyroidism or transient thyroid suppression has been reported after both single exposure and multiple exposures to iodinated contrast agents in pediatric patients 0 years to 3 years of age.

Younger age, very low birth weight, prematurity, underlying medical conditions affecting thyroid function, admission to neonatal or pediatric intensive care units, and congenital cardiac conditions are associated with an increased risk of hypothyroidism after iodinated contrast agent exposure. Pediatric patients with congenital cardiac conditions may be at greatest risk given that they often require high doses of contrast during invasive cardiac procedures.

An underactive thyroid during early life may be harmful for cognitive and neurological development and may require thyroid hormone replacement therapy. After exposure to iodinated contrast agent, individualize thyroid function monitoring based on underlying risk factors, especially in term and preterm neonates. ISOVUE-M is not indicated for use in pediatric patients younger than 2 years of age [see Use in Specific Populations (8.4)].

5.7 Hypertensive Crisis in Patients with Pheochromocytoma

Hypertensive crisis in patients with pheochromocytoma has occurred with iodinated contrast agents. Closely monitor patients when administering ISOVUE-M if pheochromocytoma or catecholamine-secreting paragangliomas are suspected. Inject the minimum amount of ISOVUE-M necessary and have measures for treatment of hypertensive crisis readily available.

5.8 Sickle Cell Crisis in Patients with Sickle Cell Disease

Iodinated contrast agents may promote sickling in individuals who are homozygous for sickle cell disease. Hydrate patients prior to and following ISOVUE-M administration and use only if the necessary imaging information cannot be obtained with alternative imaging modalities.

5.9 Severe Cutaneous Adverse Reactions

Severe cutaneous adverse reactions (SCAR) may develop from 1 hour to several weeks after administration of iodinated contrast agent. These reactions include Stevens-Johnson syndrome and toxic epidermal necrolysis (SJS/TEN), acute generalized exanthematous pustulosis (AGEP), and drug reaction with eosinophilia and systemic symptoms (DRESS). Reaction severity may increase and time to onset may decrease with repeat administration of contrast agent; prophylactic medications may not prevent or mitigate severe cutaneous adverse reactions. Avoid administering ISOVUE-M to patients with a history of a severe cutaneous adverse reaction to ISOVUE-M.

5.10 Interference with Laboratory Test

ISOVUE-M can interfere with protein-bound iodine test [see Drug Interactions (7.2)].

6 ADVERSE REACTIONS

The following adverse reactions are described in greater detail in other sections:

- Hypersensitivity Reactions [see Warnings and Precautions (5.1)]
- Acute Kidney Injury [see Warnings and Precautions (5.2)]
- Increased Risk of Seizures [see Warnings and Precautions (5.3)]
- Cardiovascular Adverse Reactions [see Warnings and Precautions (5.4)]
- Thyroid Dysfunction in Pediatric Patients 0 to 3 Years of Age [see Warnings and Precautions (5.6)]
- Severe Cutaneous Adverse Reactions [see Warnings and Precautions (5.9)]

6.1 Clinical Trials Experience

Because clinical trials are conducted under widely varying conditions, adverse reaction rates observed in the clinical trials of a drug cannot be directly compared to rates in the clinical trials of another drug and may not reflect the rates observed in practice.

The safety of ISOVUE-M was evaluated in 686 adult patients receiving ISOVUE-M intrathecally in clinical studies. Table 3 shows the common adverse reactions (>1%).

These reactions usually occur 1 to 10 hours after injection, almost all occurring within 24 hours.

Table 3: Adverse Reactions Reported in >1% of Patients Receiving Intrathecal Injection of ISOVUE-M in Clinical Studies
Adverse Reaction | ISOVUE-M (N=686) %
Headache | 16.4
Nausea | 7.3
Vomiting | 3.6
Back pain | 2.2
Leg Pain | 1.4
Neck Pain | 1.1
Hypotension | 1.1

The following additional adverse reactions occurred in ≤ 1% of patients receiving intrathecal injection of ISOVUE-M:

Cardiovascular disorder: tachycardia, hypertension, chest pain

Gastrointestinal: diarrhea, heartburn

General disorders and administration site conditions: pyrexia, muscle weakness, hot flashes, malaise, fatigue, weakness, injection site pain

Musculoskeletal: leg cramps, sciatica, cervicobrachial irritation, meningeal irritation, radicular irritation lumbosacral, other musculoskeletal pain, involuntary movement, burning sensation

Nervous system: dizziness, paresthesia, confusion, hallucinations, lightheadedness, syncope, numbness, cold extremities, ataxia, irritability

Urogenital: urinary retention

Respiratory: dyspnea

Skin and subcutaneous tissues: rash

6.2 Postmarketing Experience

The following adverse reactions have been identified during postapproval use of ISOVUE-M and other iopamidol products. Because the reactions are reported voluntarily from a population of uncertain size, it is not always possible to reliably estimate their frequency or to establish a causal relationship to drug exposure.

Blood and lymphatic system disorders: thrombocytopenia

Cardiovascular disorders: cardiopulmonary arrest, cardiac decompensation, arrhythmias, myocardial infarction, shock, electrocardiographic changes (e.g., increased QTc, increased R-R, increased T-wave amplitude), decreased systolic pressure, deep vein thrombosis, arterial spasms, transient ischemic attack, flushing, vasodilation, chest pain, pallor

Endocrine disorders: hyperthyroidism, hypothyroidism

Eye disorders: lacrimation increased, conjunctivitis, eye pruritus, transient blindness, visual disturbance, photophobia

Gastrointestinal disorders: retching, abdominal pain, salivary hypersecretion, salivary gland enlargement

General disorders and administration site conditions: chills, malaise

Immune system disorders: anaphylaxis characterized by cardiovascular, respiratory, and cutaneous manifestations (e.g., chest tightness, laryngeal edema, periorbital edema, facial edema); delayed hypersensitivity reactions including generalized maculopapular rash, erythema, pruritus, localized blistering, skin peeling

Infections and infestations: meningitis aseptic, meningitis bacterial as consequence of the procedural hazard

Musculoskeletal disorders: muscle spasm, musculoskeletal pain, muscular weakness

Nervous system: coma, seizure, tremors, syncope, cerebral edema, paralysis, depressed level of consciousness or loss of consciousness, meningism, encephalopathy

Psychiatric disorders: disorientation, agitation, restlessness, confusional state

Respiratory system disorders: respiratory arrest, respiratory failure, acute respiratory distress syndrome, respiratory distress, apnea, asthma, sneezing, choking, laryngeal edema, bronchospasm, rhinitis

Skin and subcutaneous tissue disorders: Stevens-Johnson syndrome and toxic epidermal necrolysis (SJS/TEN), acute generalized exanthematous pustulosis (AGEP), erythema multiforme and drug reaction with eosinophilia and systemic symptoms (DRESS), skin necrosis, face edema

7 DRUG INTERACTIONS

7.1 Drug-Drug Interactions

Metformin

In patients with renal impairment, metformin can cause lactic acidosis. Iodinated contrast agents appear to increase the risk of metformin-induced lactic acidosis, possibly as a result of worsening renal function. Stop metformin at the time of, or prior to, ISOVUE-M administration in patients with an eGFR between 30 and 60 mL/min/1.73 m^2 and in patients with a history of hepatic impairment, alcoholism, or heart failure. Re-evaluate eGFR 48 hours after administration of ISOVUE-M and resume metformin only after renal function is stable.

Radioactive Iodine

Administration of iodinated contrast agents may interfere with thyroid uptake of radioactive iodine (I-131 and I-123) and decrease therapeutic and diagnostic efficacy. Avoid thyroid therapy or testing for up to 6 weeks post ISOVUE-M.

7.2 Drug-Laboratory Test Interactions

Protein-Bound Iodine Test

Iodinated contrast agents will temporarily increase protein-bound iodine in blood. Avoid protein-bound iodine test for at least 16 days following administration of ISOVUE-M. However, thyroid function tests that do not depend on iodine estimations, e.g., triiodothyronine (T3) resin uptake and total or free thyroxine (T4) assays, are not affected.

8 USE IN SPECIFIC POPULATIONS

8.1 Pregnancy

Risk Summary

Available data from published literature and postmarketing cases from decades of use with iopamidol during pregnancy have not identified a drug-associated risk of major birth defects, miscarriage, or other adverse maternal or fetal outcomes. Iopamidol crosses the placenta and reaches fetal tissues in small amounts (see Data). In animal reproduction studies, no adverse developmental outcomes were observed with intravenous administration of iopamidol to pregnant rats and rabbits during organogenesis at doses up to 2.7 and 1.4 times, respectively, the maximum recommended human dose (see Data).

The background risk of major birth defects and miscarriage for the indicated population is unknown. All pregnancies have a background risk of birth defect, loss, or other adverse outcomes. In the U.S. general population, the estimated background risk of major birth defects and miscarriage in clinically recognized pregnancies is 2 to 4% and 15 to 20%, respectively.

Data

Human Data

Literature reports show that intravenously administered iopamidol crosses the placenta and is visualized in the digestive tract of exposed infants after birth.

Animal Data

Iopamidol did not affect fetal development and did not induce teratogenic changes in the offspring in either rats or rabbits at the following dose levels tested: 600 mg, 1,500 mg, or 4,000 mg iodine/kg in rats, administered intravenously once a day during days 6 through 15 of pregnancy; 300 mg, 800 mg, or 2,000 mg iodine/kg in rabbits, administered intravenously once a day during days 6 through 18 of pregnancy.

8.2 Lactation

Risk Summary

There are no data on the presence of iopamidol in human milk, the effects on the breastfed infant, or the effects on milk production. Iodinated contrast agents are present unchanged in human milk in very low amounts, with poor absorption from the gastrointestinal tract of a breastfed infant. The developmental and health benefits of breastfeeding should be considered along with the mother's clinical need for ISOVUE- M and any potential adverse effects on the breastfed infant from ISOVUE-M or from the underlying maternal condition.

Clinical Considerations

Interruption of breastfeeding after exposure to iodinated contrast agents is not necessary because the potential exposure of the breastfed infant to iodine is small. However, a lactating woman may consider interrupting breastfeeding and pumping and discarding breast milk for 10 hours (approximately 5 half- lives) after ISOVUE-M administration in order to minimize drug exposure to a breastfed infant.

8.4 Pediatric Use

The safety and effectiveness of ISOVUE-M for lumbar and thoracic myelography and CT myelography have been established in pediatric patients aged 2 years and older.

Pediatric patients at higher risk of experiencing adverse reactions during and after any iodinated contrast agent administration may include those having asthma, sensitivity to medication or allergens, cyanotic heart disease, congestive heart failure, or serum creatinine greater than 1.5 mg/dL.

Thyroid function tests indicative of thyroid dysfunction, characterized by hypothyroidism or transient thyroid suppression have been reported following iodinated contrast agent administration in pediatric patients, including term and preterm neonates; Some patients were treated for hypothyroidism. After exposure to iodinated contrast agent, individualize thyroid function monitoring in pediatric patients 0 to 3 years of age based on underlying risk factors, especially in term and preterm neonates [see Warnings and Precautions (5.6) and Adverse Reactions (6.2)].

The safety and effectiveness of ISOVUE-M for lumbar and thoracic myelography and CT myelography have not been established in pediatric patients younger than 2 years of age.

The safety and effectiveness of ISOVUE-M for cervical and total columnar myelography and CT myelography as well as for CT cisternography have not been established in pediatric patients of any age.

8.5 Geriatric Use

Iopamidol is excreted by the kidney, and the risk of adverse reactions to ISOVUE-M may be greater in patients with renal impairment. Because patients 65 years of age and older are more likely to have renal impairment, care should be taken in dose selection, and it may be useful to monitor renal function [see Warnings and Precautions (5.2) and Use in Specific Populations (8.6)].

8.6 Renal Impairment

The clearance of iopamidol decreases with increasing degree of renal impairment. In addition, preexisting renal impairment increases the risk for acute kidney injury [see Warnings and Precautions (5.2)].

10 OVERDOSAGE

Doses above 3,000 mg iodine in adults and 2,400 mg iodine in pediatric patients aged 2 years and older may result in an increased frequency and severity of adverse reactions including seizures.

Treatment of an overdose is directed toward the support of all vital functions and prompt institution of symptomatic therapy. Iopamidol can be removed by dialysis.

11 DESCRIPTION

ISOVUE-M (iopamidol) injection is a radiographic contrast agent for intrathecal use.

Iopamidol is designated chemically as (S)-N,N’-bis[2-hydroxy-1-(hydroxymethyl)-ethyl]-2,4,6- triiodo-5-lactamidoisophthalamide with a molecular weight of 777.09, an empirical formula of C17H22I3N3O8, and the following structural formula:

ISOVUE-M is a sterile, clear, colorless to pale yellow solution available in two concentrations of iodine:

- ISOVUE-M 200 mg iodine/mL: Each mL contains 408 mg iopamidol (providing 200 mg organically bound iodine) and the following inactive ingredients: 0.26 mg edetate calcium disodium (providing 0.029 mg sodium) and 1 mg tromethamine.
- ISOVUE-M 300 mg iodine/mL: Each mL contains 612 mg iopamidol (providing 300 mg organically bound iodine) and the following inactive ingredients: 0.39 mg edetate calcium disodium (providing 0.043 mg sodium) and 1 mg tromethamine.

The pH of ISOVUE-M has been adjusted to 6.5 to 7.5 with hydrochloric acid and/or sodium hydroxide.

Physicochemical characteristics are shown in Table 4. ISOVUE-M is hypertonic as compared to plasma and cerebrospinal fluid (approximately 285 and 301 mOsm/kg water, respectively).

Table 4: Physicochemical Characteristics of ISOVUE-M
Concentration (mg Iodine/mL) | 200 | 300
Osmolality @ 37°C (mOsm/kg water) | 413 | 616
Viscosity (cP) @ 37°C | 2.0 | 4.7
Viscosity (cP) @ 20°C | 3.3 | 8.8
Specific Gravity @ 37°C | 1.227 | 1.339

12 CLINICAL PHARMACOLOGY

12.1 Mechanism of Action

Intrathecal administration of iopamidol opacifies the body structures where the contrast agent is present, permitting their radiographic visualization through attenuation of photons.

12.2 Pharmacodynamics

Following intrathecal injection, iopamidol provides diagnostic contrast for at least 30 minutes for conventional myelography. At about 1 hour, contrast will no longer be sufficient for conventional myelography. However, diagnostic contrast for CT myelography remains at least 6 hours after administration. The exposure-response relationships and time course of pharmacodynamic response of iopamidol have not been fully characterized.

12.3 Pharmacokinetics

Absorption

Iopamidol is absorbed into the bloodstream from cerebrospinal fluid (CSF); following intrathecal administration, iopamidol appears in plasma within 1 hour and virtually all of the drug reaches the systemic circulation within 24 hours.

Distribution

Iopamidol did not bind to serum or plasma proteins at 1 hour after administration.

Elimination

The plasma half-life is approximately 2 hours; the half-life is not dose dependent.

Metabolism

Iopamidol does not undergo significant metabolism, deiodination, or biotransformation.

Excretion

Iopamidol is excreted mainly through the kidneys following intrathecal administration, and the drug is essentially undetectable in the plasma 48 hours later.

In patients with normal renal function, the cumulative urinary excretion for iopamidol, expressed as a percentage of administered intravenous dose is approximately 35% to 40% at 60 minutes, 80% to 90% at 8 hours, and 90% or more in the 72- to 96-hour period after administration. In patients with normal renal function, approximately 1% or less of the administered dose appears in cumulative 72- to 96-hour fecal specimens.

13 NONCLINICAL TOXICOLOGY

13.1 Carcinogenesis, Mutagenesis, Impairment of Fertility

Long-term studies in animals have not been performed with iopamidol to evaluate carcinogenic potential. No evidence of genetic toxicity was obtained in in vitro tests. In animal reproduction studies performed on rats, intravenously administered iopamidol did not induce adverse effects on fertility or general reproductive performance.

16 HOW SUPPLIED/STORAGE AND HANDLING

How Supplied

ISOVUE-M (iopamidol) injection is a clear, colorless to pale yellow solution available in the following presentations:

Concentration (mg Iodine/mL) | Package Size | Package Type | Sale Unit | NDC
200 | 10 mL | Single-Dose Vial | Carton of 10 | 0270-1411-11
300 | 15 mL | Single-Dose Vial | Carton of 10 | 0270-1412-15

Storage and Handling

Store at 20°C to 25°C (68°F to 77°F) [See USP controlled room temperature]. Protect from light.

17 PATIENT COUNSELING INFORMATION

Hypersensitivity Reactions

Advise the patient concerning the risk of hypersensitivity reactions that can occur both during and after ISOVUE-M administration. Advise the patient to report any signs or symptoms of hypersensitivity reactions during the procedure and to seek immediate medical attention for any signs or symptoms experienced after discharge [see Warnings and Precautions (5.1)].

Advise patients to inform their physician if they develop a rash after receiving ISOVUE-M [see Warnings and Precautions (5.9)].

Acute Kidney Injury

Advise the patient concerning appropriate hydration to decrease the risk of contrast induced kidney injury [see Warnings and Precautions (5.2)].

Thyroid Dysfunction

Advise parents/caregivers about the risk of developing thyroid dysfunction after ISOVUE-M administration. Advise parents/caregivers about when to seek medical care for their child to monitor for thyroid function [see Warnings and Precautions (5.6)].

Lactation

Advise lactating women that interruption of breast feeding is not necessary, however, to avoid any exposure a lactating woman may consider pumping and discarding breast milk for 10 hours after ISOVUE-M administration to minimize drug exposure to a breastfed infant [see Use in Specific Populations (8.2)].

Manufactured for:
Bracco Diagnostic Inc.
Princeton, NJ 08540
Manufactured by:
BIPSO GmbH
78224 Singen (Germany)

Revised January 2026

CL63A-07

ISOVUE-M is a registered trademark of Bracco Diagnostics Inc.

Isovue-M 200:10x 10mL Box label
NDC 0270-1411-11

Isovue-M 200: 10 mL Box internal label
NDC 0270-1411-11

Isovue-M 300:10x 15mL Box label
NDC 0270-1412-15

Isovue-M 300: 15mL Box Internal label
NDC 0270-1412-15